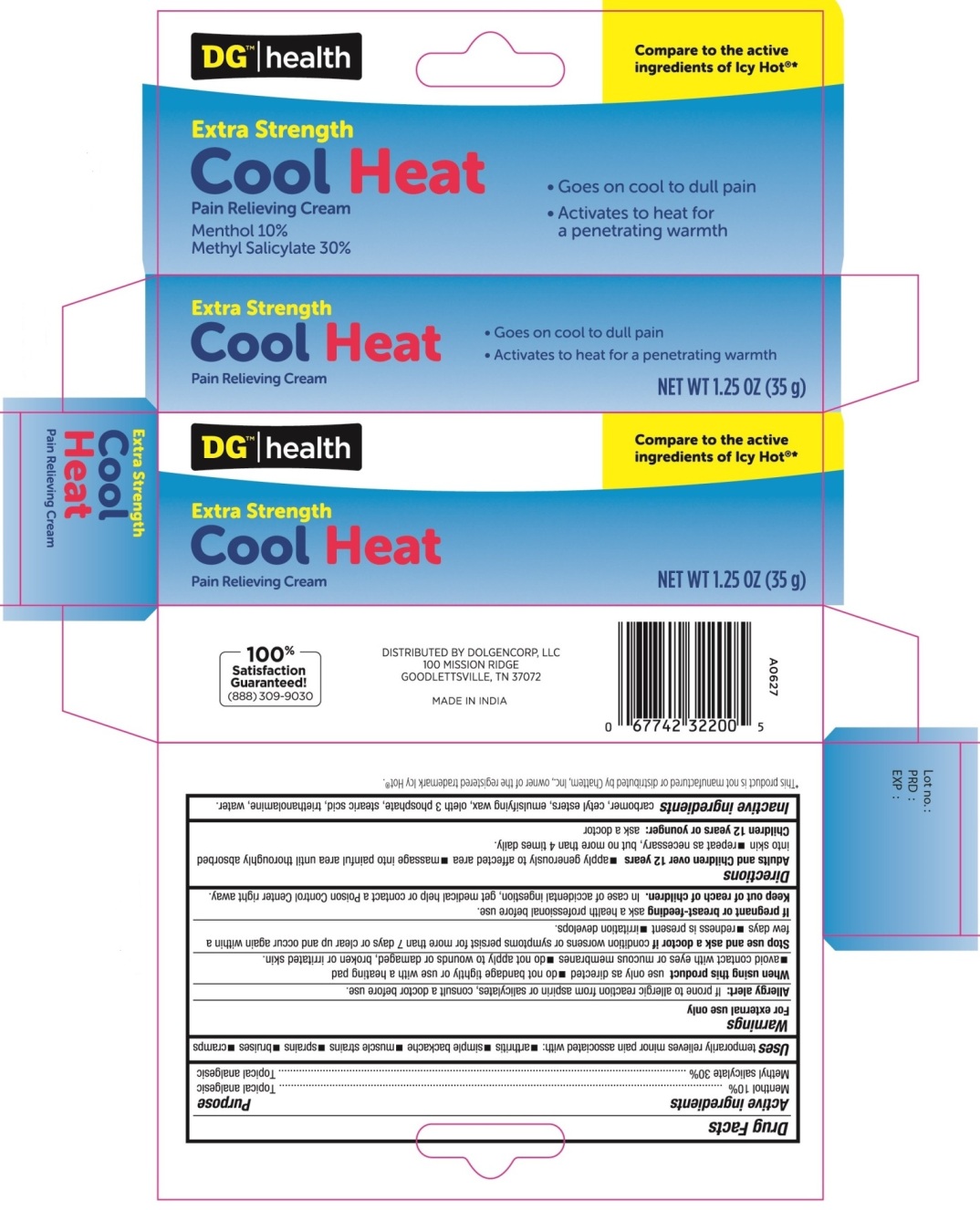 DRUG LABEL: Cool Heat
NDC: 55910-405 | Form: CREAM
Manufacturer: Dolgencorp Inc
Category: otc | Type: HUMAN OTC DRUG LABEL
Date: 20160701

ACTIVE INGREDIENTS: MENTHOL 10 g/100 g; METHYL SALICYLATE 30 g/100 g
INACTIVE INGREDIENTS: CARBOXYPOLYMETHYLENE; CETYL ESTERS WAX; OLETH-3 PHOSPHATE; STEARIC ACID; TROLAMINE; WATER

Cool Heat

Active ingredients

Menthol 10%

Methyl salicylate 30%

Purpose

Topical analgesic

Uses

temporarily relieves minor pain associated with:

- arthritis
- simple backache
- muscle strains
- sprains
- bruises
- cramps

Warnings

For external use only

Allergy alert: If prone to allergic reaction from aspirin or salicylates, consult a doctor before use.

When using this product

- use only as directed
- do not bandage tightly or use with a heating pad
- avoid contact with eyes or mucous membranes
- do not apply to wounds or damaged, broken or irritated skin

When using this product

- use only as directed
- do not bandage tightly or use with a heating pad
- avoid contact with eyes or mucous membranes
- do not apply to wounds or damaged, broken or irritated skin

PREGNANCY OR BREAST FEEDING

If pregnant or breast-feeding, ask a health care professional before use.

Keep out of reach of children.

If case of accidental ingestion, get medical help or contact a Poison Control Center right away.

Directions

Adults and Children over 12 years:

- apply generously to affected area
- massage into painful area until thoroughly absorbed into skin
- repeat as necessary, but not more than 4 times daily

Children 12 years or younger: ask a doctor

Inactive ingredients

carbomer, cetyl esters, emulsifying wax, oleth-3 phosphate, stearic acid, triethanolamine, water.

PACKAGE LABEL

PRINCIPAL DISPLAY PANEL
EXTRA STRENGTH
COOL HEAT PAIN RELIEVING CREAM
NET WT 1.25 OZ (35 g)